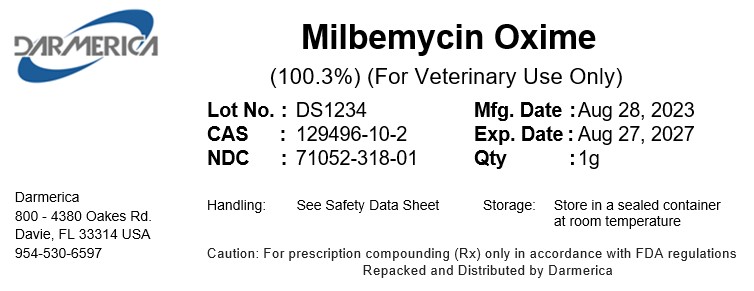 DRUG LABEL: Milbemycin Oxime
NDC: 71052-318 | Form: POWDER
Manufacturer: DARMERICA, LLC
Category: other | Type: BULK INGREDIENT - ANIMAL DRUG
Date: 20241223

ACTIVE INGREDIENTS: MILBEMYCIN OXIME 1 kg/1 kg

Milbemycin Oxime